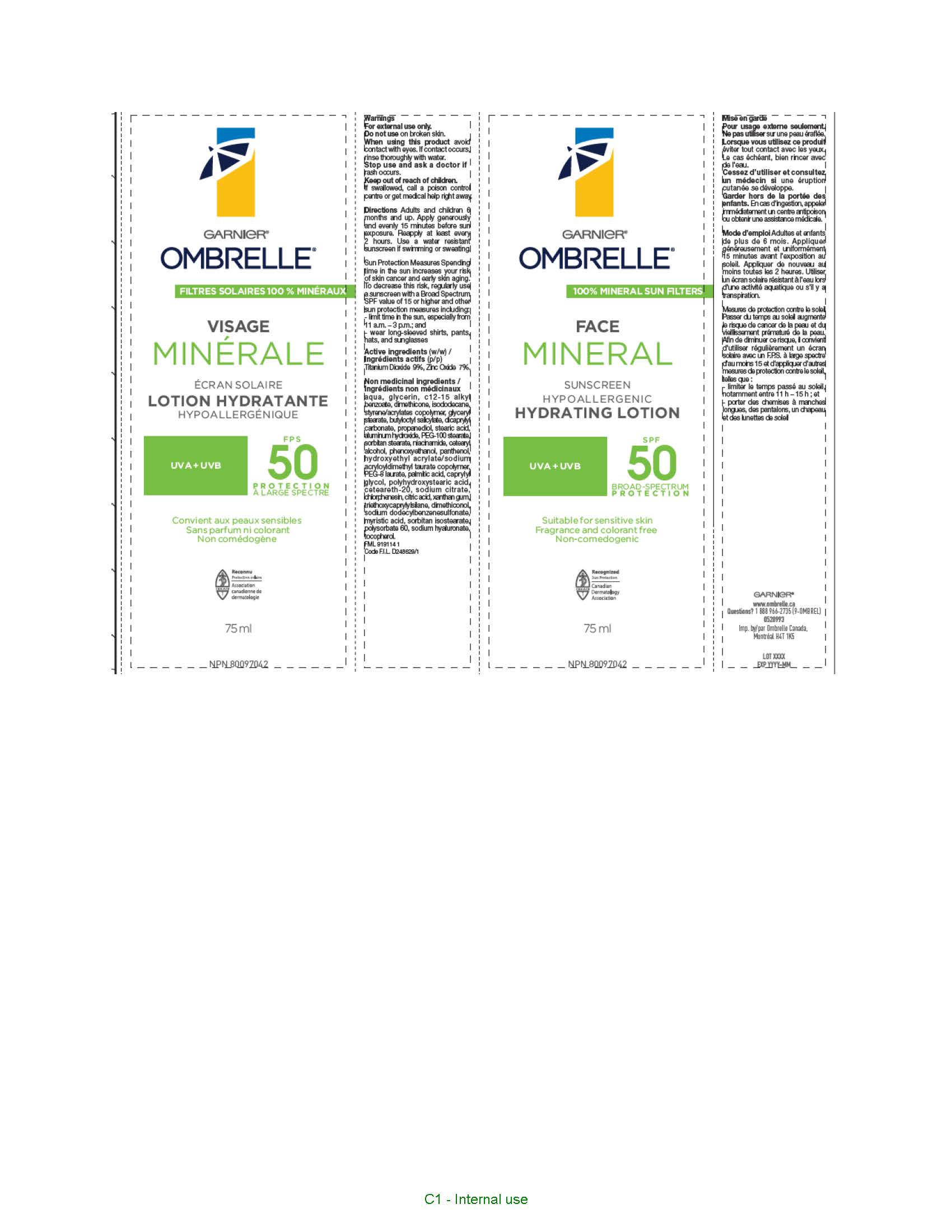 DRUG LABEL: Garnier Ombrelle Face Mineral 50
NDC: 49967-850 | Form: LOTION
Manufacturer: L'OREAL USA PRODUCTS INC
Category: otc | Type: HUMAN OTC DRUG LABEL
Date: 20260107

ACTIVE INGREDIENTS: TITANIUM DIOXIDE 90.2 mg/1 mL; ZINC OXIDE 70 mg/1 mL
INACTIVE INGREDIENTS: WATER; GLYCERIN; ALKYL (C12-15) BENZOATE; DIMETHICONE; ISODODECANE; STYRENE/ACRYLAMIDE COPOLYMER (500000 MW); GLYCERYL MONOSTEARATE; BUTYLOCTYL SALICYLATE; DICAPRYLYL CARBONATE; PROPANEDIOL; STEARIC ACID; ALUMINUM HYDROXIDE; PEG-100 STEARATE; SORBITAN MONOSTEARATE; NIACINAMIDE; CETOSTEARYL ALCOHOL; PHENOXYETHANOL; PANTHENOL; HYDROXYETHYL ACRYLATE/SODIUM ACRYLOYLDIMETHYL TAURATE COPOLYMER (100000 MPA.S AT 1.5%); PEG-8 LAURATE; PALMITIC ACID; CAPRYLYL GLYCOL; POLYHYDROXYSTEARIC ACID (2300 MW); POLYOXYL 20 CETOSTEARYL ETHER; SODIUM CITRATE; CHLORPHENESIN; CITRIC ACID MONOHYDRATE; XANTHAN GUM; TRIETHOXYCAPRYLYLSILANE; DIMETHICONOL (70 CST); SODIUM DODECYLBENZENESULFONATE; MYRISTIC ACID; SORBITAN ISOSTEARATE; POLYSORBATE 60; HYALURONATE SODIUM; TOCOPHEROL

Drug Facts

Active ingredients

Titanium dioxide 9.02%

Zinc oxide 7%

Warnings

For external use only. When using this product avoid contact witheyes. If contact occurs, rinse thoroughlly with water. Do not use on broken skin. Stop use and ask a doctor if rash occurs. Other warnings. Keep out of reach of children. If swallowed get medical help or contact a poison control center right away.

Directions

Adults and children over 6 months and up. Apply generously and evenly 15 minutes before sun exposure. Reapply at least every 2 hours. Use a water resistant sunscreen if swimming or sweating. Sun Protection measures: Spending time in the sun increases your risk of skin cancer and early skin aging. To decrease this risk, regularly use a sunscreen with a broad spectrum SPF value of 15 or higher and other sun protection measures including limit time in the sun especially from 11 a.m to 3 p.m. and wear long-sleeve shirts, pants, hats and sunglasses.

Inactive ingredients

water, glycerin, c12-15 alkyl benzoate, dimethicone, isododecane, styrene/acrylates copolymer, glyceryl stearate, butyloctyl salicylate, dicaprylyl carbonate, propanediol, stearic acid, aluminum hydroxide, PEG-100 stearate, sorbitan stearate, niacinamide, cetearyl alcohol, phenoxyethanol, panthenol, hydroxyethyl acrylate/sodium acryloyldimethyl taurate copolymer, PEG-8 laurate, palmitic acid, caprylyl glycol, polyhydroxystearic acid, ceteareth-20, sodium citrate, chlorphenesin, citric acid, xanthan gum, triethoxycaprylylsilane, dimethiconol, sodium dodecylbenzenesulfonate, myristic acid, sorbitan isostearate, polysorbate 60, sodium hyaluronate, tocopherol